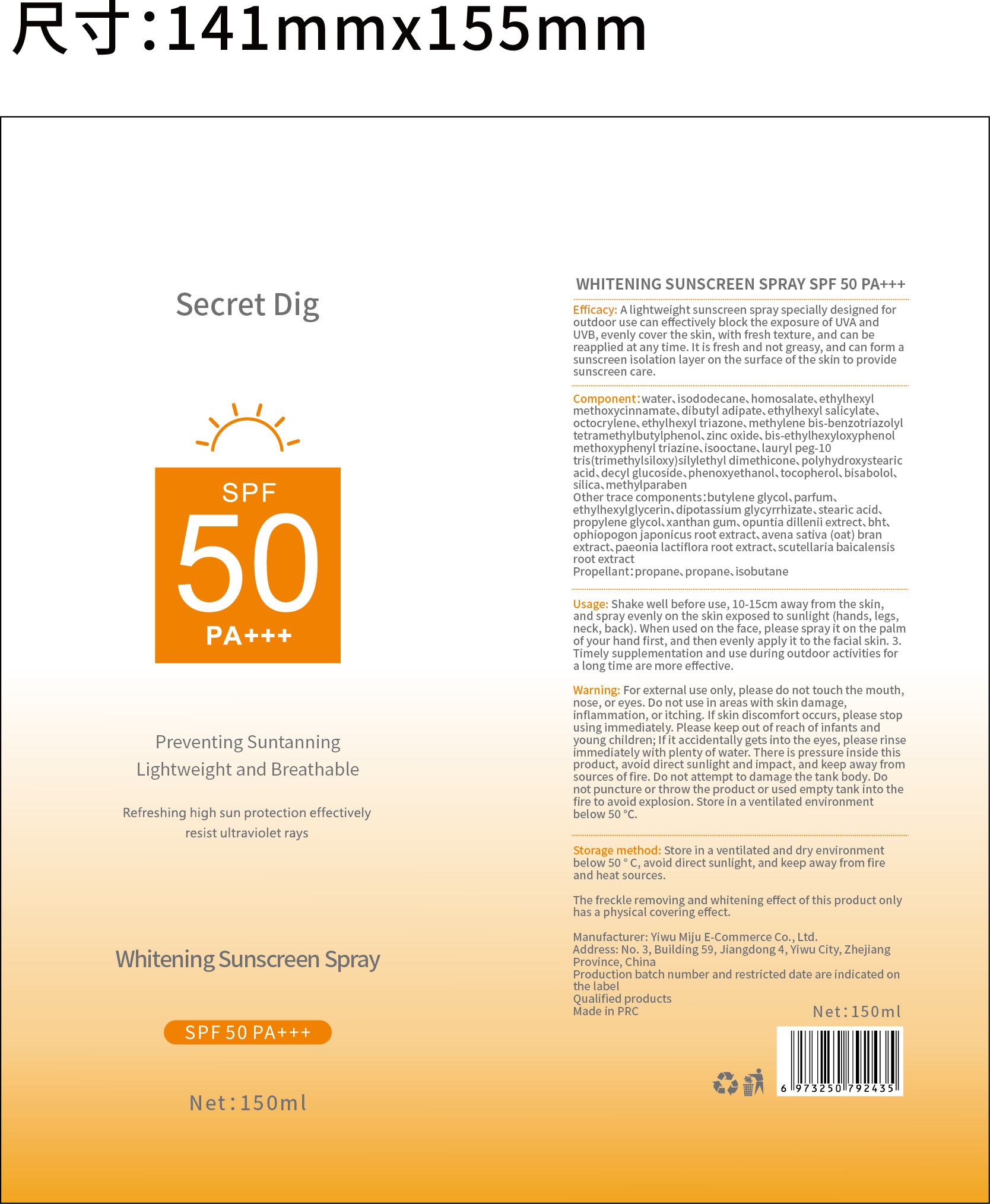 DRUG LABEL: Secret Dig Whitening Sunscreen Spray. SPF50 PA
NDC: 84462-458 | Form: AEROSOL, SPRAY
Manufacturer: Yiwu Mijue electronic Commerce Co., LTD
Category: otc | Type: HUMAN OTC DRUG LABEL
Date: 20240709

ACTIVE INGREDIENTS: HOMOSALATE 36 g/100 mL; OCTISALATE 36 g/100 mL; OCTINOXATE 20 g/100 mL
INACTIVE INGREDIENTS: DECYL GLUCOSIDE; BISOCTRIZOLE; WATER; DEHYDROXANTHAN GUM; N-SALICYLOYLGLYCINE; BEMOTRIZINOL; ETHYLHEXYL TRIAZONE; 2-PHENYLPROPANAL PROPYLENE GLYCOL ACETAL; OCTOCRYLENE; ZINC OXIDE; STEARIC ACID

84462-458 蜜掘电子

ACTIVE INGREDIENT

HOMOSALATE

OCTINOXATE

OCTISALATE

PURPOSE

A lightweight sunscreen spray specially designed foroutdoor use can effectively block the exposure of UVA andUVB,evenly cover the skin, with fresh texture, and can breapplied at any time.lt is fresh and not greasy, and can formsunscreen isolation layer on the surface of the skin to providesunscreen care.

INDICATIONS AND USAGE

A lightweight sunscreen spray specially designed for outdoor use can effectively block the exposure of UVA and UVB

Usage:Shake well before use,10-15cm away from the skin and spray evenly on the skin exposed to sunlight(hands,legs,neck,back)

DOSAGE AND ADMINISTRATION

Store in a ventilated and dry environmen below 50 °c, avoid direct sunlight, and keep away from fire and heat sources.

Net:150ml

KEEP OUT OF REACH OF CHILDREN

Please keep out of reach of infants and young children

RECENT MAJOR CHANGES

Store in a ventilated and dry environmen below 50 °c, avoid direct sunlight, and keep away from fire and heat sources.

Net:150ml

WARNINGS

Warning:For external use only,please do not ch e mouh,nose or eyes,do not use in areas with skin damage inflammation or itching

INACTIVE INGREDIENT

DECYL GLUCOSIDE

BISOCTRIZOLE

WATER

DEHYDROXANTHAN GUM

N-SALICYLOYLGLYCINE

BEMOTRIZINOL

ETHYLHEXYL TRIAZONE

2-PHENYLPROPANAL PROPYLENE GLYCOL ACETAL

OCTOCRYLENE

ZINC OXIDE

STEARIC ACID